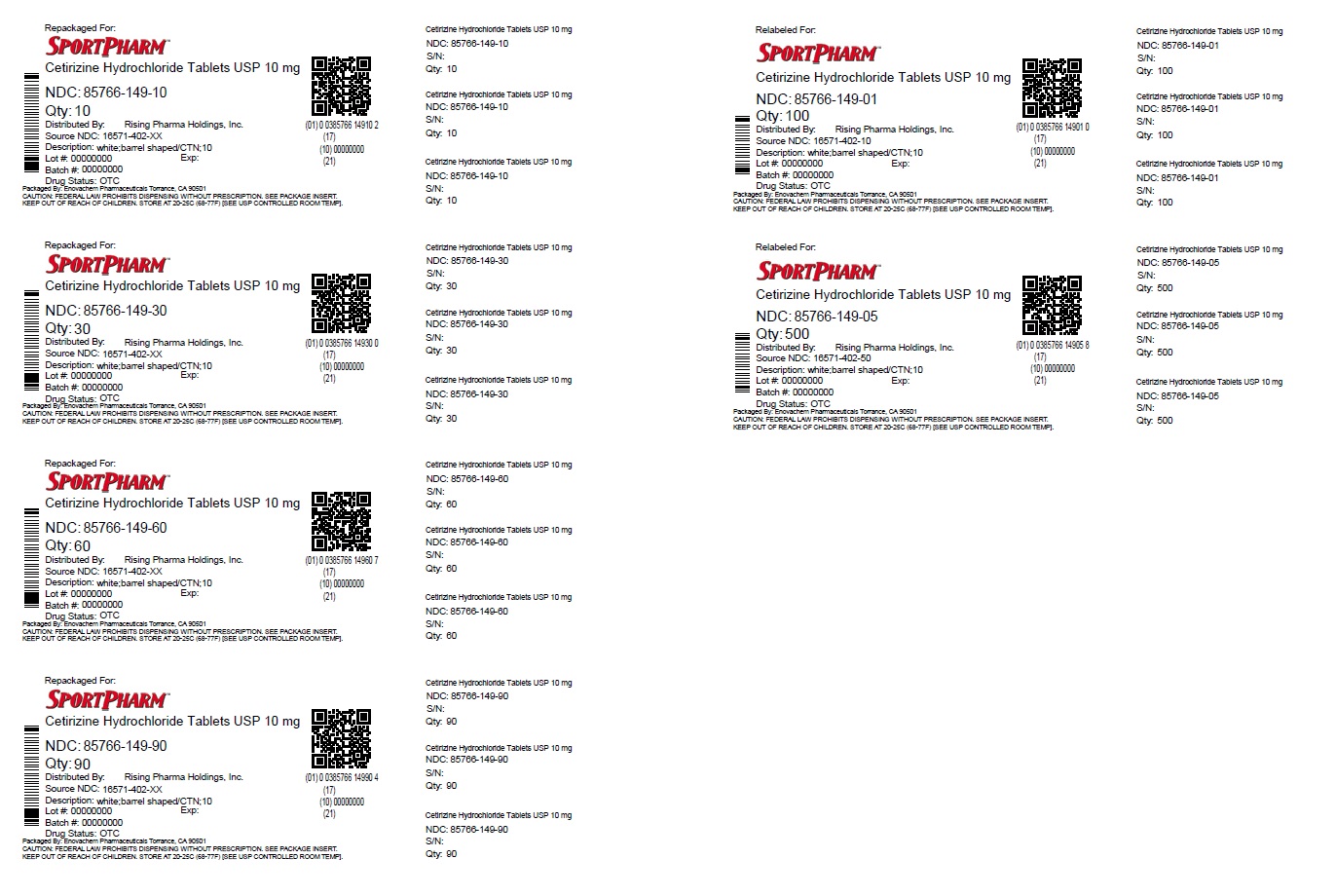 DRUG LABEL: Cetirizine Hydrochloride
NDC: 85766-149 | Form: TABLET
Manufacturer: Sportpharm LLC
Category: otc | Type: HUMAN OTC DRUG LABEL
Date: 20260206

ACTIVE INGREDIENTS: CETIRIZINE HYDROCHLORIDE 10 mg/1 1
INACTIVE INGREDIENTS: HYPROMELLOSES; LACTOSE; MAGNESIUM STEARATE; STARCH, CORN; POLYETHYLENE GLYCOL; POVIDONE; TITANIUM DIOXIDE

Cetirizine Hydrochloride Tablets USP, 10 mg, Allergy

Active Ingredient (in each tablet)

Cetirizine HCl USP 10 mg

Purpose

Antihistamine

Uses:

Temporarily relieves these symptoms due to hay fever or other upper respiratory allergies

- runny nose
- sneezing
- itchy, watery eyes
- itching of the nose or throat

Warnings:

Do Not Useif you have ever had an allergic reaction to this product or any of its ingredients or to an antihistamine containing hydroxyzine.

Ask a doctor before use if you haveliver or kidney disease. Your doctor should determine if you need a different dose.

Ask a doctor or pharmacist before use if you aretaking tranquilizers or sedatives.

When using this product

- drowsines may occur
- avoid alcoholic drinks
- alcohol, sedatives, and tranquilizers may increase drowsiness
- be careful when driving a motor vehicle or operating machinary.

Stop use and ask a doctorif an allergic reaction tothis product occurs. Seek medical help right away.

If pregnant or breast-feeding:

- if breast-feeding: not recommended
- if pregnant: ask a health professional before use.

Keep out of reach of children.

In case of overdose, get medical help or contact a Poison Control Center right away. (1-800-222-1222)

Directions

Adults and children 6 years and over | one 10 mg tablet once daily, do not take more than one 10 mg tablet in 24 hours. A 5 mg product may be appropriate for less severe symptoms.
Adults 65 years and over | Ask a doctor
Children under 6 years of age | Ask a doctor
Consumers with liver or kidney disease | Ask a doctor

Other Information:

store at 20° to 25°C (68° to 77°F)

[See USP Controlled Room Temperature].

Inactive ingredients

Hypromellose, lactose, magnesium stearate, maize starch, polyethylene glycol, povidone, titanium dioxide.

Questions?

Call 1-844-874-7464

Distributed by:

Sportpharm LLC

379 Van Ness Ave 1401,

Torrance, CA 90501

Relabeled and Repackaged by:

Enovachem PHARMACEUTICALS

Torrance, CA 90501